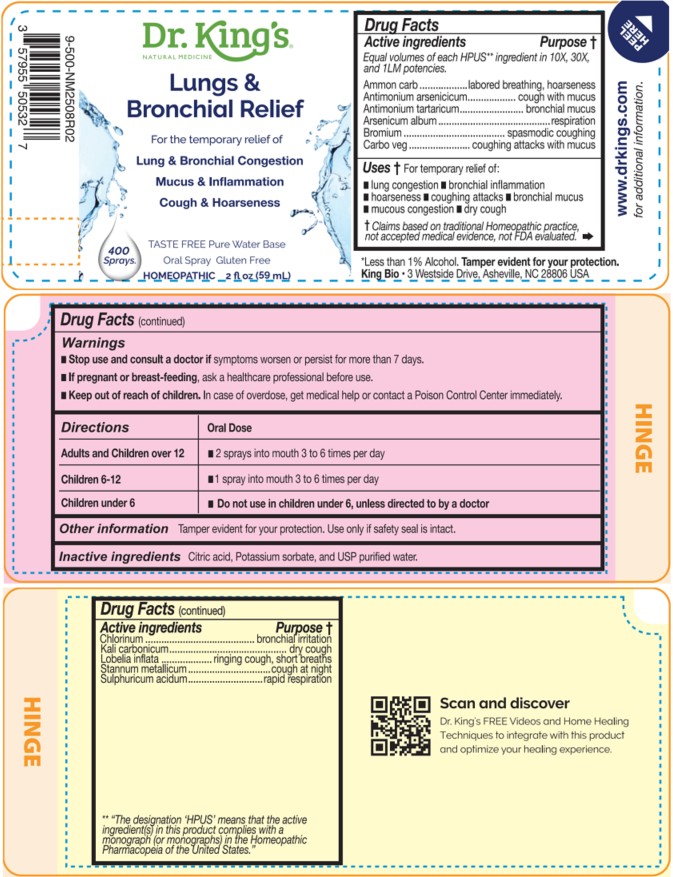 DRUG LABEL: Lungs and Bronchial Relief
NDC: 57955-9991 | Form: LIQUID
Manufacturer: King Bio Inc.
Category: homeopathic | Type: HUMAN OTC DRUG LABEL
Date: 20260302

ACTIVE INGREDIENTS: AMMONIUM CARBONATE 10 [hp_X]/59 mL; ANTIMONY ARSENATE 10 [hp_X]/59 mL; ANTIMONY POTASSIUM TARTRATE 10 [hp_X]/59 mL; ARSENIC TRIOXIDE 10 [hp_X]/59 mL; BROMINE 10 [hp_X]/59 mL; ACTIVATED CHARCOAL 10 [hp_X]/59 mL; CHLORINE 10 [hp_X]/59 mL; POTASSIUM CARBONATE 10 [hp_X]/59 mL; LOBELIA INFLATA WHOLE 10 [hp_X]/59 mL; TIN 10 [hp_X]/59 mL; SULFURIC ACID 10 [hp_X]/59 mL
INACTIVE INGREDIENTS: ANHYDROUS CITRIC ACID; POTASSIUM SORBATE; WATER

Lungs and Bronchial Relief

Active Ingredient

Equal volumes of each HPUS** ingredient in 10X,
30X, and 1LM potencies.

Ammonium carb, Antimonium arsenicicum, Antimonium tartaricum, Arsenicum album, Bromium, Carbo veg, Chlorinum, Kali carbonicum, Lobelia inflata, Stannum metallicum, Sulphuricum acidum.

** "The designation 'HPUS’ means that the active ingredient(s) in this product complies with a monograph (or Monographs) in the Homeopathic Pharmacopeia of the United States.″

INDICATIONS AND USAGE

Uses † for temporary relief of:

- lung congestion
- bronchial inflammation
- hoarseness
- coughing attacks
- bronchial mucus
- mucous congestion
- dry cough

† Claims based on traditional Homeopathic practice, not accepted medical evidence, not
FDA evaluated.

Questions

Lungs and Bronchial Relief

Taste free, Pure Water Base*

Oral Spray Gluten Free

HOMEOPATHIC 2 fl oz (59 mL)

*Less than 1% Alcohol Tamper evident for your protection.

King Bio • 3 Westside Drive, Asheville, NC 28806 USA

www.DrKings.comwww.DrKings.com for additional information.

Scan and discover Dr. King's FREE Videos and Home Healing
Techniques to integrate with this product and optimize your healing experience.

Warnings

- Stop use and consult a doctor if symptoms worsen or persist for more than 7 days.
- If pregnant or breast-feeding, ask a healthcare professional before use.

- Keep out of reach of children. In case of overdose, get medical help or contact a Poison Control Center immediately.

Directions

Directions | Oral Dose
Adults and Children over 12 | - 2 sprays into mouth 3 to 6 times per day
Children 6-12 | - 1 spray into mouth 3 to 6 times per day
Children under 6 | - Do not use in children under 6, unless directed to by a doctor

Other information

Tamper evident for your protection. Use only if safety seal is intact

Inactive Ingredients

Citric acid, Potassium sorbate, and USP purified water.

PURPOSE

Equal volumes of each HPUS ingredient in 10X, 30X, and 1LM
potencies.

Active ingredients Purpose †

Ammonium carb...........................................labored breathing, hoarseness

Antimonium arsenicicum................................................cough with mucus

Antimonium tartaricum....................................................bronchial mucus

Arsenicum album....................................................................respiration

Bromium..................................................................spasmodic coughing

Carbo veg.................................................... coughing attacks with mucus

Chlorinum...................................................................bronchial irritation

Kali carbonicum......................................................................dry cough

Lobelia inflata................................................ringing cough, short breaths

Stannum metallicum..........................................................cough at night

Sulphuricum acidum.......................................................rapid respiration

** "The designation 'HPUS’ means that the active ingredient(s) in this product complies with a monograph (or Monographs) in the Homeopathic Pharmacopeia of the United States.″

† Claims based on traditional Homeopathic practice, not accepted medical evidence, not
FDA evaluated.